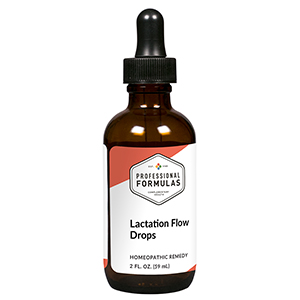 DRUG LABEL: Lactation Flow Drops
NDC: 63083-2149 | Form: LIQUID
Manufacturer: Professional Complementary Health Formulas
Category: homeopathic | Type: HUMAN OTC DRUG LABEL
Date: 20190815

ACTIVE INGREDIENTS: ARTEMISIA ANNUA FLOWERING TOP 3 [hp_X]/59 mL; CHASTE TREE FRUIT 6 [hp_X]/59 mL; OYSTER SHELL CALCIUM CARBONATE, CRUDE 6 [hp_X]/59 mL; ANHYDROUS DIBASIC CALCIUM PHOSPHATE 6 [hp_X]/59 mL; BOS TAURUS HYPOTHALAMUS 6 [hp_X]/59 mL; BOS TAURUS LYMPH VESSEL 6 [hp_X]/59 mL; SUS SCROFA MAMMARY GLAND 6 [hp_X]/59 mL; BOS TAURUS PITUITARY GLAND, POSTERIOR 6 [hp_X]/59 mL; SODIUM BORATE 9 [hp_X]/59 mL; FERULA ASSA-FOETIDA RESIN 12 [hp_X]/59 mL; SKIM MILK 12 [hp_X]/59 mL; LACTUCA VIROSA WHOLE 12 [hp_X]/59 mL; PULSATILLA MONTANA WHOLE 12 [hp_X]/59 mL; RICINUS COMMUNIS SEED 12 [hp_X]/59 mL; CLAVICEPS PURPUREA SCLEROTIUM 12 [hp_X]/59 mL; LOBARIA PULMONARIA 12 [hp_X]/59 mL; URTICA URENS WHOLE 12 [hp_X]/59 mL
INACTIVE INGREDIENTS: ALCOHOL; WATER

C149

ACTIVE INGREDIENTS

Chamomilla 3X
Agnus castus 6X
Calcarea carbonica 6X
Calcarea phosphorica 6X
Hypothalamus 6X
Lymph 6X
Mammary 6X
Pituitary 6X
Borax 9X
Asafoetida 12X
Lac defloratum 12X
Lactuca virosa 12X
Pulsatilla 12X
Ricinus communis 12X
Secale cornutum 12X
Sticta pulmonaria 12X
Urtica urens 12X

QUESTIONS

Professional Formulas

PO Box 2034 Lake Oswego, OR 97035

INDICATIONS

For temporary assistance with inadequate lactation.*

PURPOSE

*Claims based on traditional homeopathic practice, not accepted medical evidence. Not FDA evaluated.

WARNINGS

In case of overdose, get medical help or contact a poison control center right away.

Keep out of the reach of children.

PREGNANCY OR BREAST FEEDING

If pregnant or breastfeeding, ask a healthcare professional before use.

DIRECTIONS

Place drops under tongue 30 minutes before/after meals. Adults and children 12 years and over: Take 10 drops up to 3 times per day. Consult a physician for use in children under 12 years of age.

OTHER INFORMATION

Tamper resistant. If seal is broken, do not use. After opening, close container tightly and store at room temperature away from heat.

INACTIVE INGREDIENTS

20% ethanol, purified water.

LABEL

Est 1985

Professional Formulas

Complementary Health

Lactation Flow Drops

Homeopathic Remedy

2 FL. OZ. (59 mL)